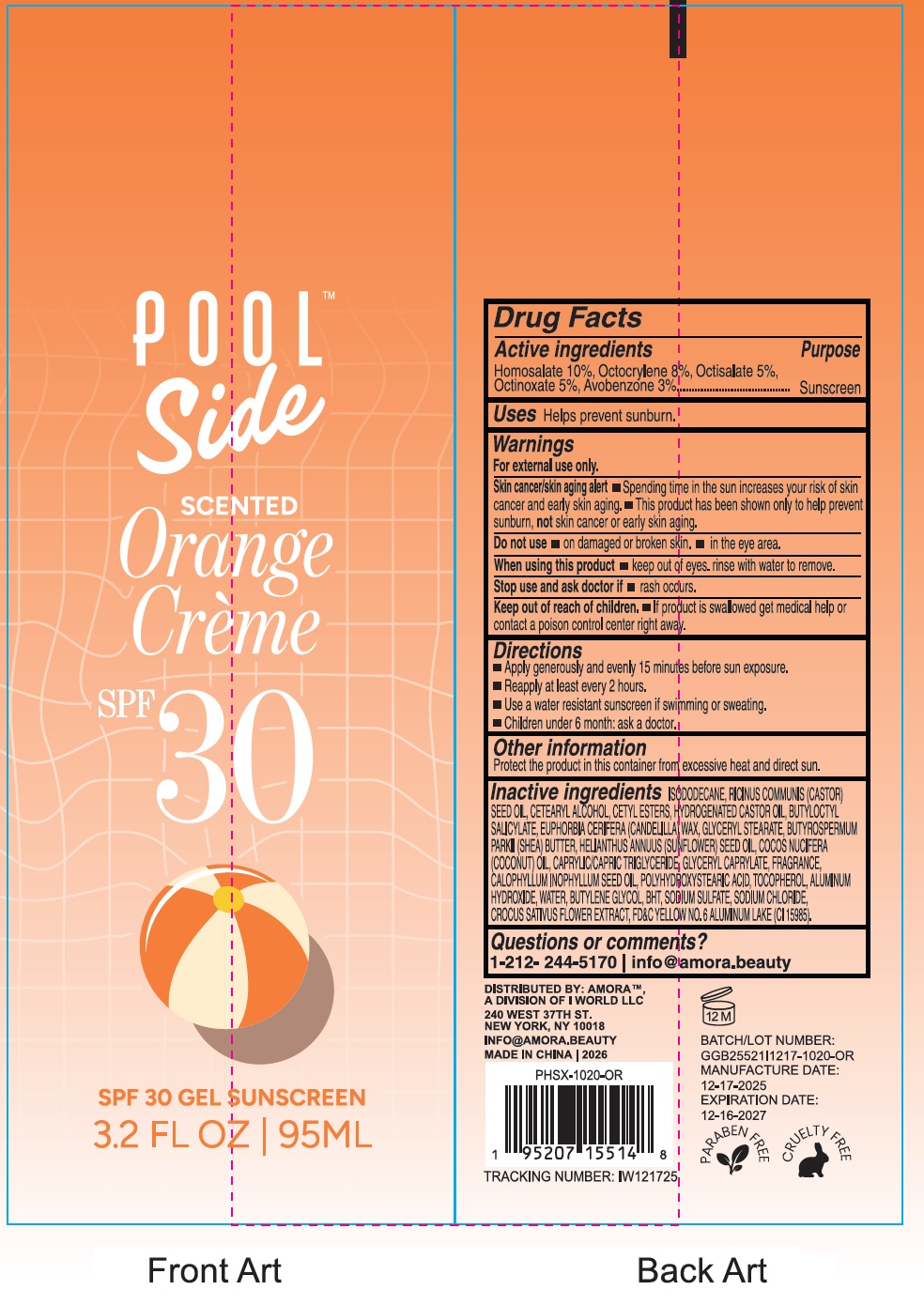 DRUG LABEL: Poolside Orange Creme SPF 30 Scented Sunscreen
NDC: 85179-028 | Form: LIQUID
Manufacturer: I World LLC
Category: otc | Type: HUMAN OTC DRUG LABEL
Date: 20260109

ACTIVE INGREDIENTS: HOMOSALATE 100 mg/1 mL; OCTOCRYLENE 80 mg/1 mL; OCTISALATE 50 mg/1 mL; OCTINOXATE 50 mg/1 mL; AVOBENZONE 30 mg/1 mL
INACTIVE INGREDIENTS: ISODODECANE; CASTOR OIL; CETOSTEARYL ALCOHOL; CETYL ESTERS WAX; HYDROGENATED CASTOR OIL; BUTYLOCTYL SALICYLATE; CANDELILLA WAX; GLYCERYL MONOSTEARATE; SHEA BUTTER; SUNFLOWER OIL; COCONUT OIL; MEDIUM-CHAIN TRIGLYCERIDES; GLYCERYL MONOCAPRYLATE; TAMANU OIL; TOCOPHEROL; ALUMINUM HYDROXIDE; WATER; BUTYLENE GLYCOL; BUTYLATED HYDROXYTOLUENE; SODIUM SULFATE; SODIUM CHLORIDE; CROCUS SATIVUS FLOWER; FD&C YELLOW NO. 6

Poolside Orange Creme SPF 30 Scented Gel Sunscreen

Active ingredients

Homosalate 10%, Octocrylene 8%, Octisalate 5%, Octinoxate 5%, Avobenzone 3%

Purpose

Sunscreen

Uses

Helps prevent sunburn.

Warnings

For external use only.

Skin cancer/skin aging alert

- Spending time in the sun increases your risk of skin cancer and early skin aging.
- This product has been shown only to help prevent sunburn, not skin cancer or early skin aging.

Do not use

- on damaged or broken skin.

When using this product

- keep out of eyes. rinse with water to remove.

Stop use and ask doctor if

- rash occurs.

Keep out of reach of children.

- If product is swallowed get medical help or contact a poison control center right away.

Directions

- Apply generously and evenly 15 minutes before sun exposure.
- Reapply at least every 2 hours.
- Use a water resistant sunscreen if swimming or sweating.
- Children under 6 month: ask a doctor.

Other information

Protect the product in this container from excessive heat and direct sun.

Inactive Ingredients

ISODODECANE, RICINUS COMMUNIS (CASTOR) SEED OIL, CETEARYL ALCOHOL, CETYL ESTERS, HYDROGENATED CASTOR OIL, BUTYLOCTYL SALICYLATE, EUPHORBIA CERIFERA (CANDELILLA) WAX, GLYCERYL STEARATE, BUTYROSPERMUM PARKII (SHEA) BUTTER, HELIANTHUS ANNUUS (SUNFLOWER) SEED OIL, COCOS NUCIFERA (COCONUT) OIL, CAPRYLIC/CAPRIC TRIGLYCERIDE, GLYCERYL CAPRYLATE, FRAGRANCE, CALOPHYLLUM INOPHYLLUM SEED OIL, POLYHYDROXYSTEARIC ACID, TOCOPHEROL, ALUMINUM HYDROXIDE, WATER, BUTYLENE GLYCOL, BHT, SODIUM SULFATE, SODIUM CHLORIDE, CROCUS SATIVUS FLOWER EXTRACT, FD&C YELLOW NO.6 ALUMINUM LAKE (CI 15985).

Questions or comments?

1-212- 244-5170 info@amora.beauty